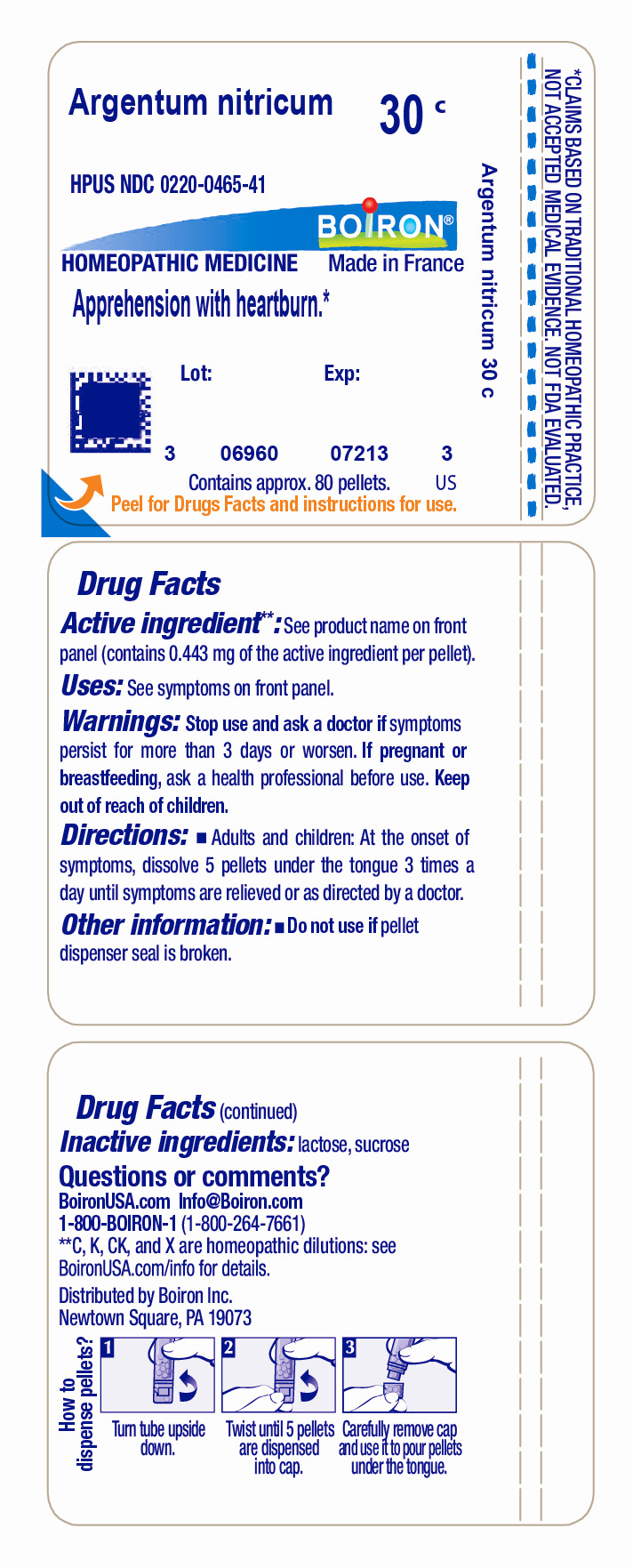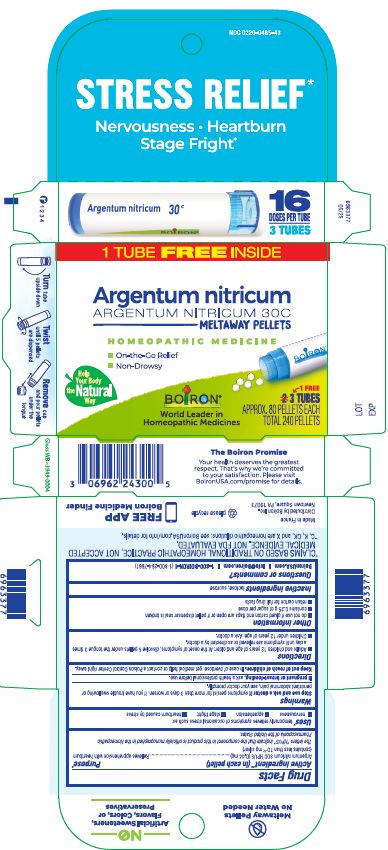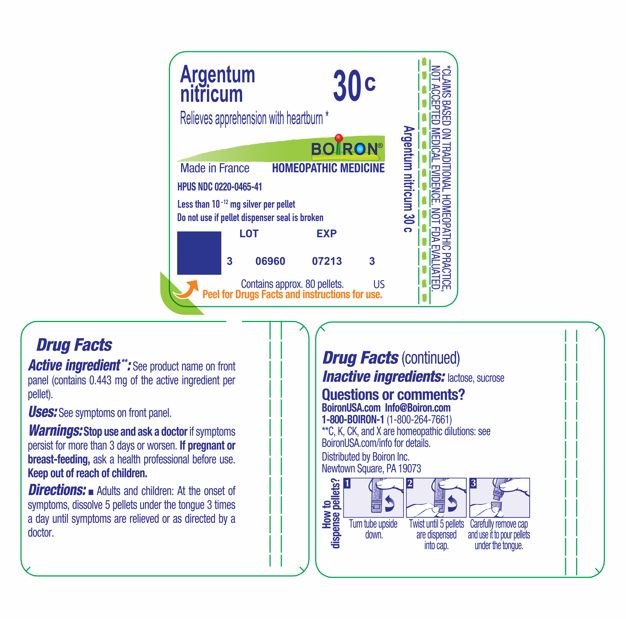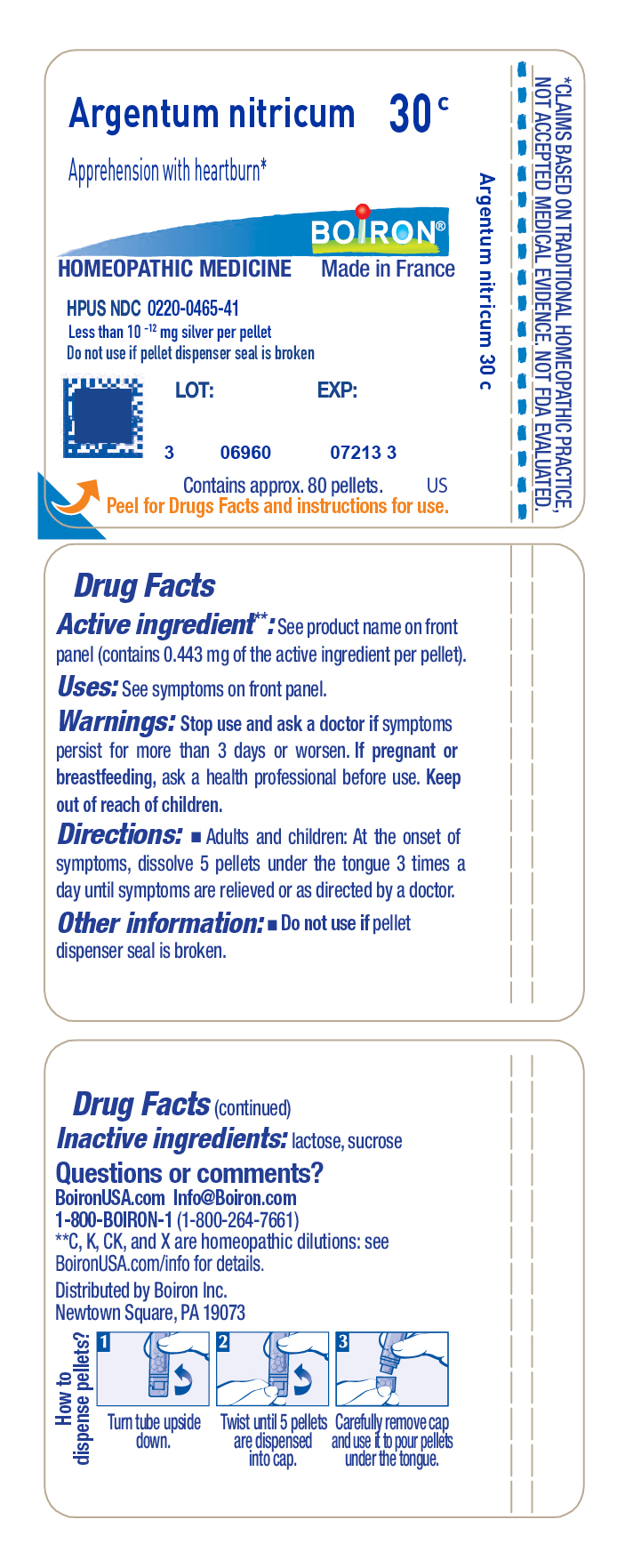 DRUG LABEL: Argentum nitricum
NDC: 0220-0465 | Form: PELLET
Manufacturer: Boiron
Category: homeopathic | Type: HUMAN OTC DRUG LABEL
Date: 20250923

ACTIVE INGREDIENTS: SILVER NITRATE 30 [hp_C]/30 [hp_C]
INACTIVE INGREDIENTS: SUCROSE; LACTOSE, UNSPECIFIED FORM

Argentum nitricum 30C

Active ingredient** (in each pellet)

Argentum nitricum 30C HPUS (0.44 mg)

(contains less than 10^-12 mg silver)

The letters “HPUS” indicate that the component in this product is officially monographed in the Homeopathic Pharmacopoeia of the United States.

Purpose*

Argentum nitricum 30C HPUS (0.44 mg)…………….…Relieves apprehension with heartburn

Uses*

temporarily relieves symptoms of occasional stress such as:

▪ nervousness ▪ apprehension ▪ stage fright ▪ heartburn caused by stress

Stop use and ask a doctor if symptoms persist for more than 3 days or worsen. If you have trouble swallowing or persistent abdominal pain, see your doctor promptly.

PREGNANCY OR BREAST FEEDING

If pregnant or breast-feeding, ask a health professional before use.

Keep out of reach of children. In case of overdose, get medical help or contact a Poison Control Center right away.

DOSAGE AND ADMINISTRATION

- Adults and children 12 years of age and older: At the onset of symptoms, dissolve 5 pellets under the tongue 3 times a day until symptoms are relieved or as directed by a doctor.
- Children under 12 years of age: Ask a doctor.

INACTIVE INGREDIENT

lactose, sucrose

QUESTIONS

BoironUSA.com

Info@Boiron.com

1-800-BOIRON-1 (1-800-264-7661)

Made in France

Distributed by Boiron Inc.

Newtown Square, PA 19073

- do not use if glued carton end flaps are open or if pellet dispenser seal is broken
- contains 0.25 g of sugar per dose
- retain carton for full drug facts

3 TUBES

APPROX. 80 PELLETS EACH

TOTAL 240 PELLETS

16 DOSES PER TUBE

STRESS RELIEF*

Do not use if pellet dispenser seal is broken.
Contains approx 80 pellets.
How to dispense pellets? Turn tube upside down. Twist until 5 pellets are dispensed into cap. Carefully remove the cap and use it to pour pellets under the tongue.
*CLAIMS BASED ON TRADITIONAL HOMEOPATHIC PRACTICE NOT ACCEPTED MEDICAL EVIDENCE. NOT FDA EVALUATED.
*C,K,CK, and X are homeopathic dilutions: see BoironUSA.com/info for details.